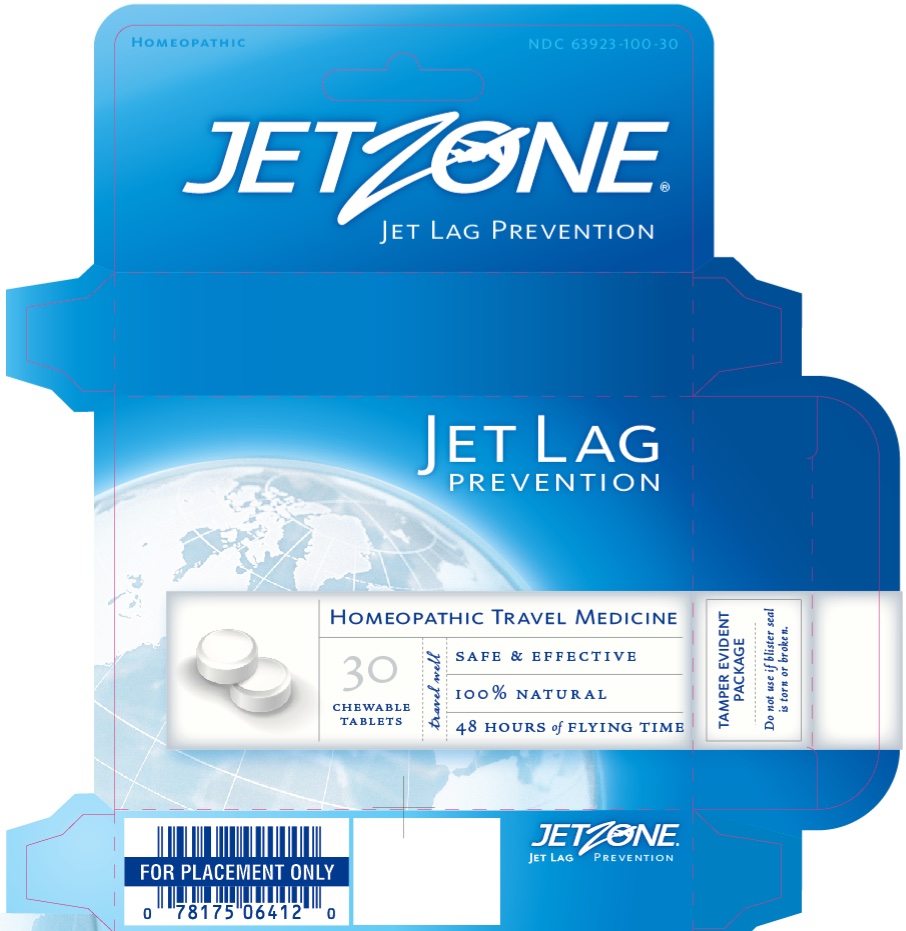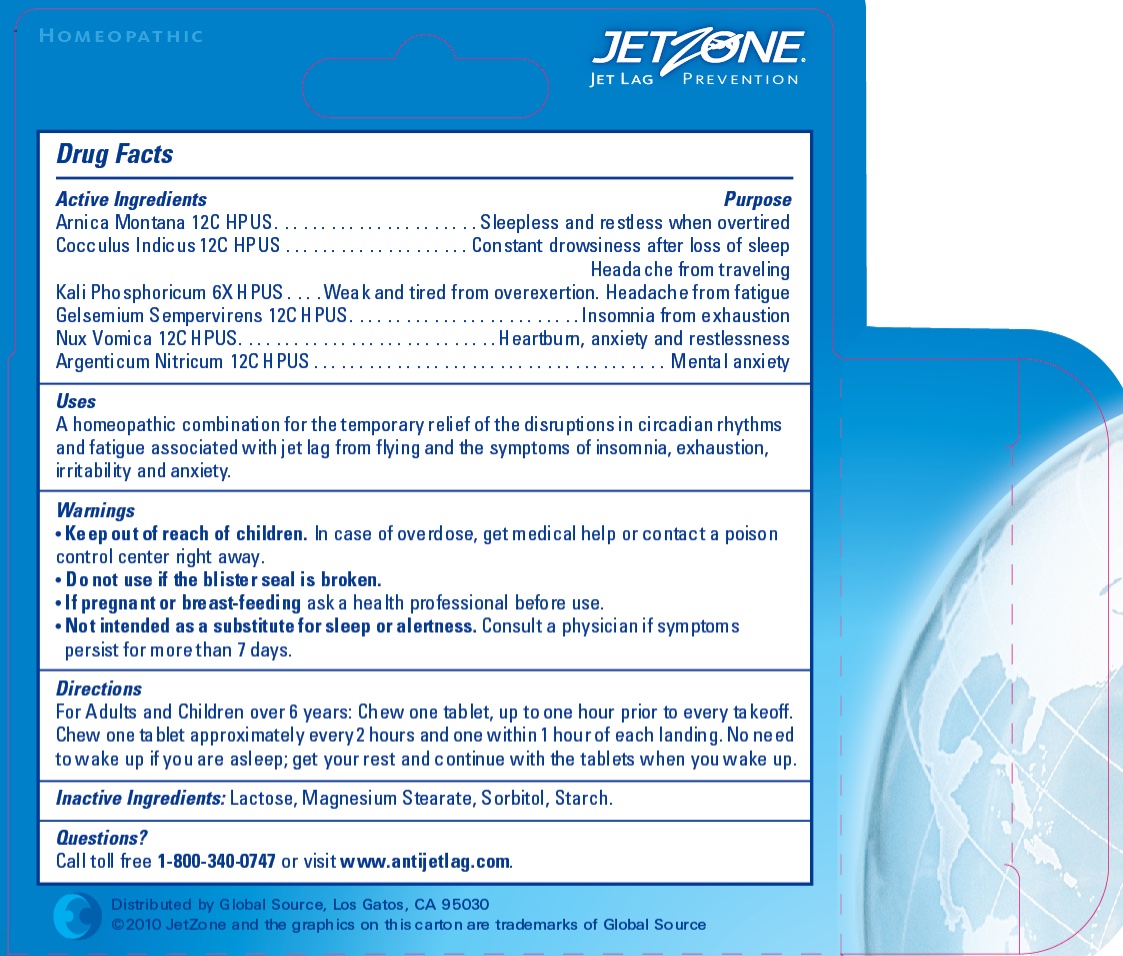 DRUG LABEL: JetZone Jet Lag Prevention
NDC: 63923-100 | Form: TABLET, CHEWABLE
Manufacturer: Belclare Corporation
Category: homeopathic | Type: HUMAN OTC DRUG LABEL
Date: 20241101

ACTIVE INGREDIENTS: GELSEMIUM SEMPERVIRENS ROOT 12 [hp_C]/1 1; ANAMIRTA COCCULUS SEED 12 [hp_C]/1 1; ARNICA MONTANA 12 [hp_C]/1 1; STRYCHNOS NUX-VOMICA WHOLE 12 [hp_C]/1 1; SILVER NITRATE 12 [hp_C]/1 1; POTASSIUM PHOSPHATE, DIBASIC 6 [hp_X]/1 1
INACTIVE INGREDIENTS: MAGNESIUM STEARATE; LACTOSE; SORBITOL; STARCH, CORN

JetZone Jet Lag Prevention

Active Ingredients

Arnica montana 12C HPUS

Cocculus indicus 12C HPUS
Kali Phosphoricum 6X HPUS
Gelsemium Sempervirens 12C HPUS
Nux Vomica 12C HPUS

Argenticum Nitricum 12C HPUS

Purpose*

Arnica montana - Sleepless and restless when overtired

Cocculus indicus - Constant drowsiness after loss of sleep. Headache from traveling

Kali Phosphoricum - Weak and tired from overexertion. Headache from fatigue
Gelsemium Sempervirens - Insomnia from exhaustion
Nux Vomica - Heartbum, anxiety and restlessness

Argenticum Nitricum - Mental anxiety

Uses

A homeopathic combination for the temporary relief of the disruptions in circadian rhythms and fatigue associated with jet lag from flying and the symptoms of insomnia, exhaustion, irritability and anxiety.

WARNINGS

Do not use if the blister seal is broken.

PREGNANCY OR BREAST FEEDING

If pregnant or breast-feeding,ask a health professional before use.

Keep out of reach of children.In case of overdose, get medical help or contact a Poison Control Center right away.

WHEN USING

Not intended as a substitute for sleep or alertness. Consult a physician if symptoms persist for more than 7 days.

Directions

For Adults and Children over 6 years: Chew one tablet, up to one hour prior to every takeoff.

Chew one ta blet approximately every 2 hours and one within 1 hour of each landing. No need to wake up if you are asleep; get your rest and continue with the tablets when you wake up.

Inactive ingredients

Lactose, Magnesium Stearate, Sorbitol, Starch.

Question?

Questions?

Call toll free 1-800-340-0747 or visit www.antijetlag.com